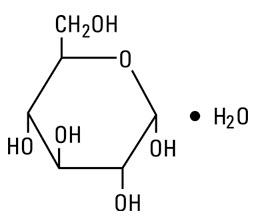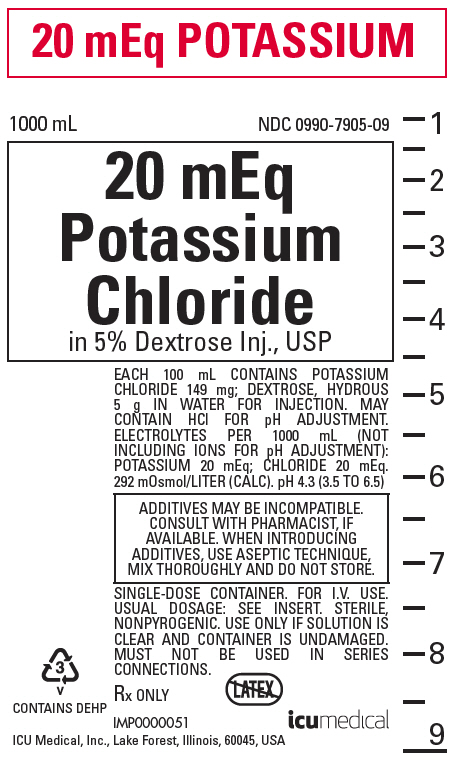 DRUG LABEL: Potassium Chloride in Dextrose
NDC: 0990-7905 | Form: INJECTION, SOLUTION
Manufacturer: ICU Medical Inc.
Category: prescription | Type: HUMAN PRESCRIPTION DRUG LABEL
Date: 20251030

ACTIVE INGREDIENTS: DEXTROSE MONOHYDRATE 5 g/100 mL; POTASSIUM CHLORIDE 0.149 g/100 mL
INACTIVE INGREDIENTS: WATER; HYDROCHLORIC ACID

POTASSIUM CHLORIDE
in Dextrose Injection, USP

20 mEq/liter Potassium Chloride in 5% Dextrose Injection

Rx only

DESCRIPTION

Potassium Chloride in Dextrose Injection, USP is a sterile and nonpyrogenic solution in water for injection. This solution is for administration by intravenous infusion only.

See Table for summary of content and characteristics of this solution.

This solution contains no bacteriostat, antimicrobial agent or added buffer and is intended only for use as a single-dose injection. When smaller doses are required the unused portion should be discarded.

This solution is a parenteral fluid, nutrient and electrolyte replenisher.

Dextrose, USP is chemically designated D-glucose monohydrate (C6H12O6 ∙ H2O), a hexose sugar freely soluble in water. It has the following structural formula:

Potassium Chloride, USP is chemically designated KCl, a white granular powder freely soluble in water.

Water for Injection, USP is chemically designated H2O.

The flexible plastic container is fabricated from a specially formulated polyvinyl chloride. Water can permeate from inside the container into the overwrap but not in amounts sufficient to affect the solution significantly. Solutions in contact with the plastic container may leach out certain chemical components from the plastic in very small amounts; however, biological testing was supportive of the safety of the plastic container materials. Exposure to temperatures above 25°C/77°F during transport and storage will lead to minor losses in moisture content. Higher temperatures lead to greater losses. It is unlikely that these minor losses will lead to clinically significant changes within the expiration period.

CLINICAL PHARMACOLOGY

When administered intravenously, this solution provides a source of water and potassium chloride with carbohydrate.

Solutions containing carbohydrate in the form of dextrose restore blood glucose levels and provide calories. Carbohydrate in the form of dextrose may aid in minimizing liver glycogen depletion and exerts a protein-sparing action. Dextrose injected parenterally undergoes oxidation to carbon dioxide and water.

Intravenous solutions containing potassium chloride are particularly intended to provide needed potassium cation (K^+). Potassium is the chief cation of body cells (160 mEq/liter of intracellular water). It is found in low concentration in plasma and extracellular fluids (3.5 to 5.0 mEq/liter in a healthy adult). Potassium plays an important role in electrolyte balance. Normally about 80 to 90% of the potassium intake is excreted in the urine; the remainder in the stools and to a small extent, in the perspiration. The kidney does not conserve potassium well so that during fasting or in patients on a potassium-free diet, potassium loss from the body continues resulting in potassium depletion. A deficiency of either potassium, or chloride will lead to a deficit of the other.

Water is an essential constituent of all body tissues and accounts for approximately 70% of total body weight. Average normal adult daily requirement ranges from two to three liters (1.0 to 1.5 liters each for insensible water loss by perspiration and urine production).

Water balance is maintained by various regulatory mechanisms. Water distribution depends primarily on the concentration of electrolytes in the body compartments and sodium (Na^+) plays a major role in maintaining physiologic equilibrium.

INDICATIONS AND USAGE

This solution is indicated in patients requiring parenteral administration of potassium chloride with minimal carbohydrate calories.

CONTRAINDICATIONS

Solutions containing potassium chloride are contraindicated in diseases where high potassium levels may be encountered.

WARNINGS

Solutions which contain potassium ions should be used with great care, if at all, in patients with hyperkalemia, severe renal failure and in conditions in which potassium retention is present.

To avoid potassium intoxication, do not infuse these solutions rapidly. In patients with severe renal insufficiency or adrenal insufficiency, administration of potassium chloride may cause potassium intoxication.

In patients with diminished renal function, administration of solutions containing potassium ions may result in potassium retention.

The intravenous administration of this solution can cause fluid and/or solute overloading resulting in dilution of serum electrolyte concentrations, overhydration, congested states or pulmonary edema.

The risk of dilutional states is inversely proportional to the electrolyte concentration of administered parenteral solutions. The risk of solute overload causing congested states with peripheral and pulmonary edema is directly proportional to the electrolyte concentrations of such solutions.

PRECAUTIONS

Clinical evaluation and periodic laboratory determinations are necessary to monitor changes in fluid balance, electrolyte concentrations and acid-base balance during prolonged parenteral therapy or whenever the condition of the patient warrants such evaluation.

Solutions containing dextrose should be used with caution in patients with known subclinical or overt diabetes mellitus.

Caution must be exercised in the administration of parenteral fluids, especially those containing sodium ions, to patients receiving corticosteroids or corticotropin.

Potassium replacement therapy should be guided primarily by serial electrocardiograms. Plasma potassium levels are not necessarily indicative of tissue potassium levels.

High plasma concentrations of potassium may cause death through cardiac depression, arrhythmias or arrest.

Potassium-containing solutions should be used with caution in the presence of cardiac disease, particularly in digitalized patients or in the presence of renal disease.

Care should be exercised to insure that the needle (or catheter) is well within the lumen of the vein and that extravasation does not occur.

Do not administer unless solution is clear and container is undamaged. Discard unused portion.

Pregnancy Category C

Animal reproduction studies have not been conducted with dextrose or potassium chloride. It is also not known whether dextrose or potassium chloride can cause fetal harm when administered to a pregnant woman or can affect reproduction capacity. Dextrose or potassium chloride should be given to a pregnant woman only if clearly needed.

Pediatric use

The safety and effectiveness in the pediatric population are based on the similarity of the clinical conditions of the pediatric and adult populations. In neonates or very small infants the volume of fluid may affect fluid and electrolyte balance.

Frequent monitoring of serum glucose concentrations is required when dextrose is prescribed to pediatric patients, particularly neonates and low birth weight infants.

In very low birth weight infants, excessive or rapid administration of dextrose injection may result in increased serum osmolality and possible intracerebral hemorrhage.

ADVERSE REACTIONS

Reactions which may occur because of the solutions or technique of administration include febrile response, infection at the site of injection, venous thrombosis or phlebitis extending from the site of injection, extravasation and hypervolemia.

If an adverse reaction does occur, discontinue the infusion, evaluate the patient, institute appropriate therapeutic countermeasures and save the remainder of the fluid for examination if deemed necessary.

Nausea, vomiting, abdominal pain and diarrhea have been reported with potassium therapy. The signs and symptoms of potassium intoxication include paresthesias of the extremities, flaccid paralysis, listlessness, mental confusion, weakness and heaviness of the legs, hypotension, cardiac arrhythmias, heart block, electrocardiographic abnormalities such as disappearance of P waves, spreading and slurring of the QRS complex with development of a biphasic curve and cardiac arrest.

Potassium-containing solutions are intrinsically irritating to tissues. Therefore, extreme care should be taken to avoid perivascular infiltration. Local tissue necrosis and subsequent sloughing may result if extravasation occurs. Chemical phlebitis and venospasm have also been reported.

Should perivascular infiltration occur, I.V. administration at that site should be discontinued at once. Local infiltration of the affected area with procaine hydrochloride, 1%, to which hyaluronidase may be added, will often reduce venospasm and dilute the potassium remaining in the tissues locally. Local application of heat may also be helpful.

OVERDOSAGE

In the event of potassium overdosage, discontinue the infusion immediately and institute intensive corrective therapy to reduce serum potassium levels. See WARNINGS and PRECAUTIONS.

DOSAGE AND ADMINISTRATION

This solution should be administered only by intravenous infusion and as directed by the physician. The dose and rate of injection are dependent upon the age, weight and clinical condition of the patient. If the serum potassium level is greater than 2.5 mEq/liter, potassium should be given at a rate not to exceed 10 mEq/hour in a concentration less than 30 mEq/liter. Somewhat faster rates and greater concentrations (usually up to 40 mEq/liter) of potassium may be indicated in patients with more severe potassium deficiency. The total 24-hour dose should not generally exceed 200 mEq of potassium.

As reported in the literature, the dosage and constant infusion rate of intravenous dextrose must be selected with caution in pediatric patients, particularly neonates and low birth weight infants, because of the increased risk of hyperglycemia/hypoglycemia.

Parenteral drug products should be inspected visually for particulate matter and discoloration prior to administration, whenever solution and container permit. See PRECAUTIONS.

Drug Interactions

Additives may be incompatible. Consult with pharmacist, if available. When introducing additives, use aseptic technique, mix thoroughly and do not store.

INSTRUCTIONS FOR USE

To Open

Tear outer wrap at notch and remove solution container. If supplemental medication is desired, follow directions below before preparing for administration. Some opacity of the plastic due to moisture absorption during the sterilization process may be observed. This is normal and does not affect the solution quality or safety. The opacity will diminish gradually.

To Add Medication

1. Prepare additive port.
2. Using aseptic technique and an additive delivery needle of appropriate length, puncture resealable additive port at target area, inner diaphragm and inject. Withdraw needle after injecting medication.
3. The additive port may be protected by covering with an additive cap.
4. Mix container contents thoroughly.

Preparation for Administration
(Use aseptic technique)

1. Close flow control clamp of administration set.
2. Remove cover from outlet port at bottom of container.
3. Insert piercing pin of administration set into port with a twisting motion until the set is firmly seated. NOTE: When using a vented administration set, replace bacterial retentive air filter with piercing pin cover. Insert piercing pin with twisting motion until shoulder of air filter housing rests against the outlet port flange.
4. Suspend container from hanger.
5. Squeeze and release drip chamber to establish proper fluid level in chamber.
6. Attach venipuncture device to set.
7. Open clamp to expel air from set and venipuncture device. Close clamp.
8. Perform venipuncture.
9. Regulate rate of administration with flow control clamp.

WARNING: Do not use flexible container in series connections.

HOW SUPPLIED

Potassium Chloride in Dextrose Injection, USP solution is supplied in single-dose flexible plastic containers. See Table:

Table of Contents and Characteristics
 |  |  | Grams/100 mL |  | Per 1000 mL
mEq Potassium | Size (mL) | NDC No. | Dextrose Hydrous | Potassium Chloride | Potassium (K+) | Chloride (Cl¯) | Caloric Value | Calculated Osmolarity (mOsmol) | Tonicity | pH
20 mEq | 1000 | 0409–7905–09 | 5 | 0.149 | 20 mEq | 20 mEq | 170 | 292 | isotonic | 4.3 (3.5 to 6.5)
20 mEq | 1000 | 0990–7905–09 | 5 | 0.149 | 20 mEq | 20 mEq | 170 | 292 | isotonic | 4.3 (3.5 to 6.5)

ICU Medical is transitioning NDC codes from the "0409" to "0990" labeler code. Both NDC codes are expected to be in the market for a period of time.

May contain HCl for pH adjustment.

STORAGE AND HANDLING

Store at 20 to 25°C (68 to 77°F). [See USP Controlled Room Temperature.] Protect from freezing.

Revised: March, 2020

IFU0000169

ICU Medical, Inc., Lake Forest, Illinois, 60045, USA

icumedical

PRINCIPAL DISPLAY PANEL - 1000 mL Bag Label

20 mEq POTASSIUM

1000 mL
NDC 0990-7905-09

20 mEq
Potassium
Chloride
in 5% Dextrose Inj., USP

EACH 100 mL CONTAINS POTASSIUM
CHLORIDE 149 mg; DEXTROSE, HYDROUS
5 g IN WATER FOR INJECTION. MAY
CONTAIN HCl FOR pH ADJUSTMENT.
ELECTROLYTES PER 1000 mL (NOT
INCLUDING IONS FOR pH ADJUSTMENT):
POTASSIUM 20 mEq; CHLORIDE 20 mEq.
292 mOsmol/LITER (CALC). pH 4.3 (3.5 TO 6.5)

ADDITIVES MAY BE INCOMPATIBLE.
CONSULT WITH PHARMACIST, IF
AVAILABLE. WHEN INTRODUCING
ADDITIVES, USE ASEPTIC TECHNIQUE,
MIX THOROUGHLY AND DO NOT STORE.

SINGLE-DOSE CONTAINER. FOR I.V. USE.
USUAL DOSAGE: SEE INSERT. STERILE,
NONPYROGENIC. USE ONLY IF SOLUTION IS
CLEAR AND CONTAINER IS UNDAMAGED.
MUST NOT BE USED IN SERIES
CONNECTIONS.

Rx ONLY

3
v
CONTAINS DEHP

IMP0000051
ICU Medical, Inc., Lake Forest, Illinois, 60045, USA

icumedical